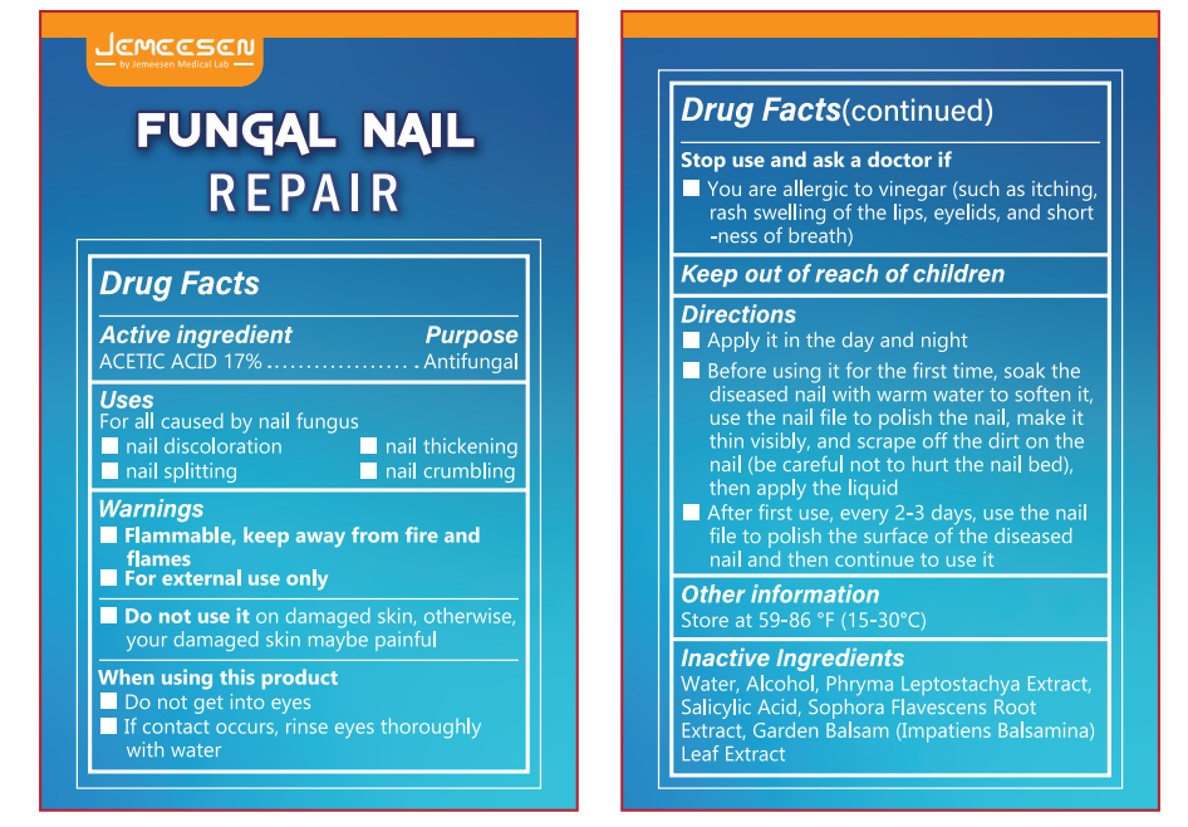 DRUG LABEL: FUNGAL NAIL REPAIR
NDC: 84445-001 | Form: LIQUID
Manufacturer: Shenzhen Furuizhilian keji Co., Ltd.
Category: otc | Type: HUMAN OTC DRUG LABEL
Date: 20240626

ACTIVE INGREDIENTS: ACETIC ACID 17 g/100 mL
INACTIVE INGREDIENTS: ALCOHOL; WATER; SALICYLIC ACID; SOPHORA FLAVESCENS ROOT; PHRYMA LEPTOSTACHYA WHOLE; IMPATIENS BALSAMINA LEAF

FUNGAL NAIL REPAIR

ACTIVE INGREDIENT

ACETIC ACID 17%

PURPOSE

Antifungal

Keep out ofreach ofchildren

INDICATIONS AND USAGE

For all caused by nail fungus
nail discoloration
nail thickening
nail splitting
nail crumbling

WARNINGS

Flammable, keep away from fire and flames
For external use only

DOSAGE AND ADMINISTRATION

Apply it in the day and night
Before using it for the first time, soak thediseased nail with warm water to soften it,use the nail file to polish the nail, make itthin visibly, and scrape off the dirt on thenail (be careful not to hurt the nail bed),then apply the liquid
After first use, every 2-3 days, use the nailfille to polish the surface of the diseasednail and then continue to use it

STORAGE AND HANDLING

Store at 59-86 °F(15-30°C)

INACTIVE INGREDIENT

Water, Alcohol, Phryma Leptostachya Extract,Salicylic Acid, Sophora Flavescens RootExtract, Garden Balsam (Impatiens Balsamina)Leaf Extract